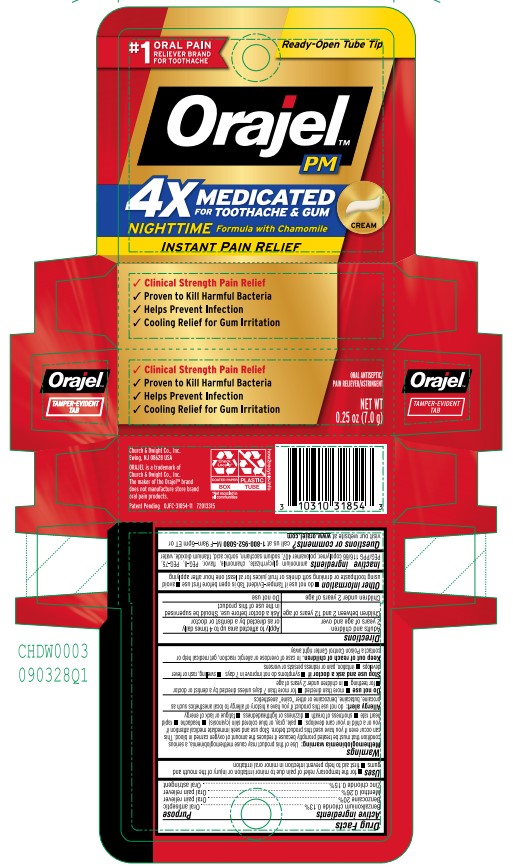 DRUG LABEL: Orajel 4X Medicated PM For Toothache and Gum
NDC: 10237-789 | Form: CREAM
Manufacturer: Church & Dwight Co., Inc.
Category: otc | Type: HUMAN OTC DRUG LABEL
Date: 20251212

ACTIVE INGREDIENTS: BENZOCAINE 200 mg/1 g; BENZALKONIUM CHLORIDE 1.3 mg/1 g; ZINC CHLORIDE 1.5 mg/1 g; MENTHOL, UNSPECIFIED FORM 2.6 mg/1 g
INACTIVE INGREDIENTS: PEG-75 LANOLIN; METHYL SALICYLATE; POLYETHYLENE GLYCOL 400; AMMONIUM GLYCYRRHIZATE; CHAMOMILE; POLOXAMER 407; SORBIC ACID; TITANIUM DIOXIDE; WATER; PEG/PPG-116/66 COPOLYMER; SACCHARIN SODIUM

Orajel 4X Medicated PM For Toothache and Gum, Cream

Active Ingredients

Benzalkonium chloride 0.13%

Benzocaine 20%

Menthol 0.26%

Zinc chloride 0.15%

Purpose

Oral antiseptic, Oral pain reliever, Oral astringent

Uses

- for the temporary relief of pain due to minor irritation or injury of the mouth and gums
- first aid to help prevent infection in minor oral irritation

Warnings

Methemoglobinemia warning: use of this product may cause methemoglobinemia, a serious condition that must be treated promptly because it reduces the amount of oxygen carried in blood. This can occur even if you have used this product before. Stop use and seek immediate medical attention if you or a child in your care develops: pale, gray, or blue colored skin (cyanosis), headache, rapid heart rate, shortness of breath, dizziness or lightheadedness, fatigue or lack of energy

Allergy alert: do not use this product if you have a history of allergy to local anesthetics such as procaine, butacaine, benzocaine or other "caine" anesthetics

Do not use

- more than directed
- for more than 7 days unless directed by a dentist or doctor
- for teething
- in children under 2 years of age

Stop use and ask a doctor if

- symptoms do not improve in 7 days
- swelling, rash or fever develops
- irritation, pain or redness persists or worsens

Keep out of reach of children

In case of overdose or allergic reaction, get medical help or contact a Poison Control Center right away

Directions

Adults and children 2 years of age and older

- Apply to affected area up to 4 times daily or as directed by a dentist or doctor

Children between 2 and 12 years of age

- Ask a doctor before use. Should be supervised in the use of this product

Children under 2 years of age

- Do not use

Other information

- do not use if Tamper-Evident Tab is open before first use
- avoid using toothpaste or drinking soft drinks or fruit juices for at least one hour after applying

Inactive ingredients

ammonium glycyrrhizate, chamomile, flavor, PEG-8, PEG-75, PEG/PPG 116/66 copolymer, poloxamer 407, sodium saccharin, sorbic acid, titanium dioxide, water

Questions or comments?

call us at 1-800-952-5080 M-F 9am-5pm ET or visit our website at www.orajel.com

Principal Display Panel

1 ORAL PAIN RELIEVER FOR TOOTHACHES

Ready-Open Tube Tip

Orajel

4X MEDICATED FOR TOOTHACHE AND GUM

NIGHTTIME FORMULA WITH CHAMOMILE

INSTANT PAIN RELIEF CREAM

Clinical Strength Pain Relief

Proven to Kill Harmful Bacteria

Helps Prevent Infection

Cooling Relief for Gum Irritation

ORAL ANTISEPTIC/PAIN RELIEVER/ASTRINGENT

NET WT

0.25 OZ (7.0 g)